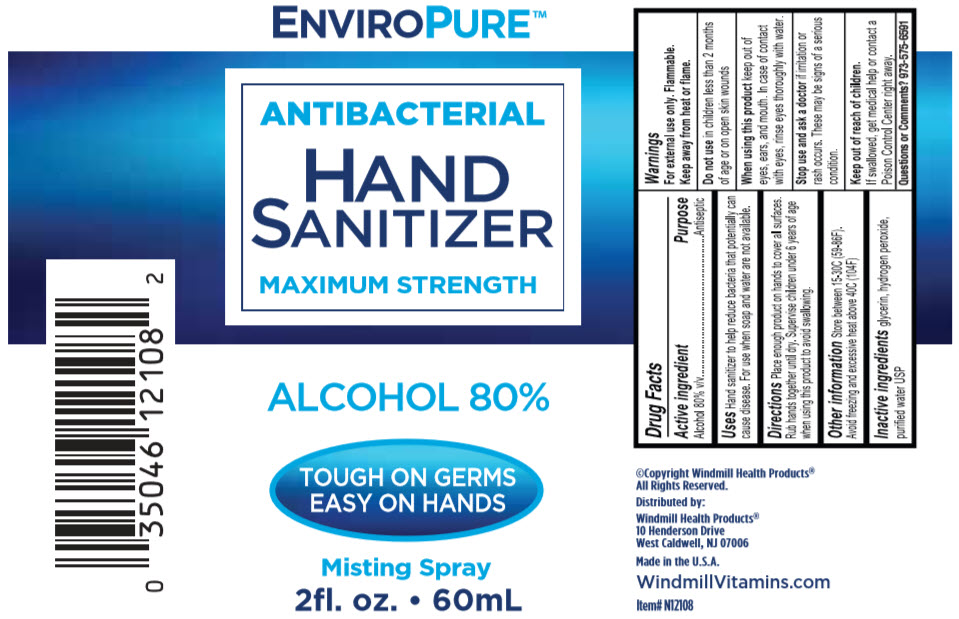 DRUG LABEL: EnviroPure Antibacterial Hand Sanitizer Maximum Strength
NDC: 74154-010 | Form: SPRAY
Manufacturer: Windmill Health Products, LLC
Category: otc | Type: HUMAN OTC DRUG LABEL
Date: 20210122

ACTIVE INGREDIENTS: Alcohol 80 mL/100 mL
INACTIVE INGREDIENTS: Glycerin; Hydrogen Peroxide; Water

EnviroPure™ Antibacterial Hand Sanitizer Maximum Strength

Drug Facts

Active Ingredients

Alcohol 80% v/v

Purpose

Antiseptic

Uses

Hand sanitizer to help reduce bacteria that potentially can cause disease. For use when soap and water are not available.

Warnings

For external use only. Flammable. Keep away from heat or flame.

Do not use in children less than 2 months of age or on open skin wounds

When using this product keep out of eyes, ears and mouth. In case of contact with eyes, rinse eyes thoroughly with water.

Stop use and ask a doctor if irritation or rash occurs. These may be signs of a serious condition.

Keep out of reach of children. If swallowed, get medical help or contact a Poison Control Center right away.

Directions

Place enough product on hands to cover all surfaces. Rub hands together until dry. Supervise children under 6 years of age when using this product to avoid swallowing.

Other information

Store between 15-30C (59-86F).

Avoid freezing and excessive heat above 40C(104F)

Inactive Ingredients

Glycerin, hydrogen peroxide, purified water USP

Questions or Comments?

973-575-6591

Distributed by:

Windmill Health Products®
10 Henderson Drive
West Caldwell, NJ 07006

PRINCIPAL DISPLAY PANEL - 60 mL Bottle Label

ENVIROPURE™

ANTIBACTERIAL

HAND
SANITIZER

MAXIMUM STRENGTH

ALCOHOL 80%

TOUGH ON GERMS
EASY ON HANDS

Misting Spray
2fl. oz. • 60mL